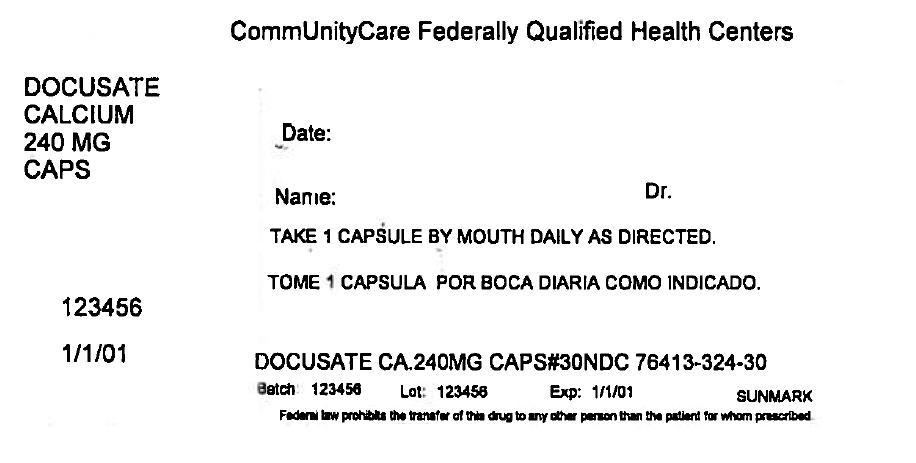 DRUG LABEL: stool softener
NDC: 76413-324 | Form: CAPSULE, LIQUID FILLED
Manufacturer: Central Texas Community Health Centers
Category: otc | Type: HUMAN OTC DRUG LABEL
Date: 20161031

ACTIVE INGREDIENTS: DOCUSATE CALCIUM 240 mg/1 1
INACTIVE INGREDIENTS: CORN OIL; D&C RED NO. 33; FD&C RED NO. 40; GELATIN, UNSPECIFIED; GLYCERIN; WATER; SORBITOL; FD&C BLUE NO. 1; FD&C YELLOW NO. 6

Drug Facts

Active ingredient (in each softgel)

Docusate calcium 240 mg

Purpose

Stool softener laxative

Uses

- for relief of occasional constipation
- this product generally produces a bowel movement within 12 to 72 hours

Warnings

Do not use

if you are currently taking mineral oil, unless directed by a doctor.

Ask a doctor before use if you have

- stomach pain
- nausea
- vomiting
- noticed a sudden change in bowel habits that lasts over 2 weeks

Stop use and ask a doctor if

- you have rectal bleeding or fail to have a bowel movement after use of a laxative. These could be signs of a serious condition.
- you need to use a laxative for more than 1 week

If pregnant or breast-feeding,

ask a health professional before use.

Keep out of reach of children.

In case of overdose, get medical help or contact a Poison Control Center right away.

Directions

- adults and children 12 years of age and over: take 1 softgel daily or as directed by a doctor
- children under 12 years of age: ask a doctor

Other information

- store at 20º-25ºC (68º-77ºF); excursions permitted between 15º-30ºC (59º-86ºF)

Inactive Ingredients

corn oil, D&C red #33*, edible white ink, FD&C blue #1*, FD&C red #40, FD&C yellow #6*, gelatin, glycerin, purified water, sorbitol special

*contains one or more of these ingredients

Questions or comments?

Call 1-877-753-3935 Monday-Friday 9AM-5PM EST

PRINCIPAL DISPLAY PANEL - 240 MG Capsule Bottle Label

CommUnityCare Federally Qualified Health Centers

DOCUSATE
CALCIUM
240 MG
CAPS

Date:

Name:
Dr.

TAKE 1 CAPSULE BY MOUTH DAILY AS DIRECTED.

123456

1/1/01

DOCUSATE CA.240MG CAPS#30NDC 76413-324-30

Batch: 123456
Lot: 123456
Exp: 1/1/01
SUNMARK

Federal law prohibits the transfer of this drug to any other person than the patient for whom prescribed.